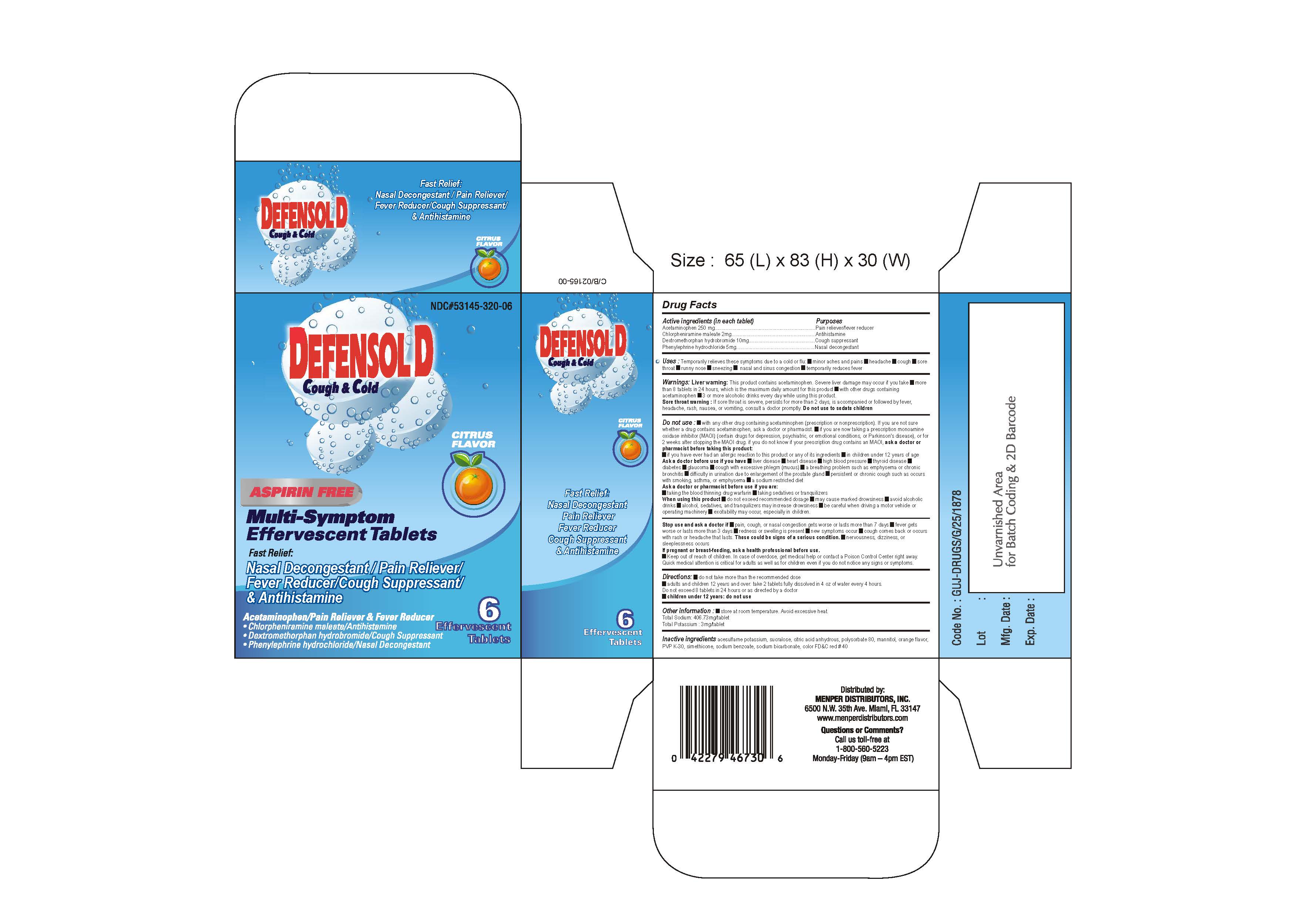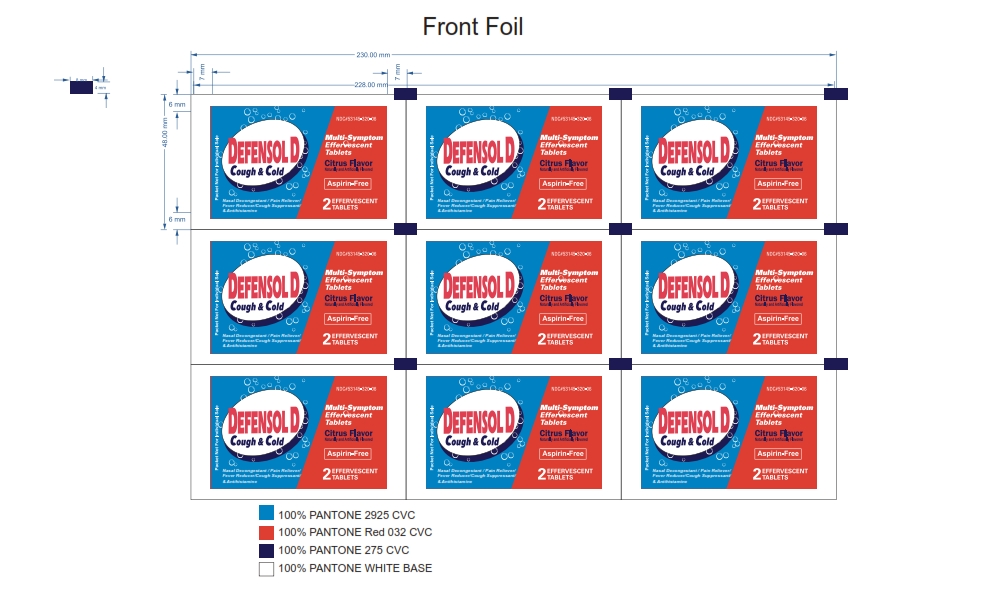 DRUG LABEL: Defensol D (Multi Symptom Effervescent Tablets)
NDC: 53145-320 | Form: TABLET, EFFERVESCENT
Manufacturer: Menper Distributors Inc.
Category: otc | Type: HUMAN OTC DRUG LABEL
Date: 20160105

ACTIVE INGREDIENTS: ACETAMINOPHEN 250 mg/250 1; CHLORPHENIRAMINE MALEATE 2 mg/250 1; DEXTROMETHORPHAN HYDROBROMIDE 10 mg/250 1; PHENYLEPHRINE HYDROCHLORIDE 5 mg/250 1
INACTIVE INGREDIENTS: ACESULFAME POTASSIUM; SUCRALOSE; ANHYDROUS CITRIC ACID; POLYSORBATE 80; MANNITOL; POVIDONE K30; PEG-9 POLYDIMETHYLSILOXYETHYL DIMETHICONE; SODIUM BENZOATE; SODIUM BICARBONATE; FD&C RED NO. 40

Defensol D (Multi Symptom Effervescent Tablets)

Active Ingredients

Active Ingredients (in each tablet) Purposes
Acetaminophen 250 mg…………………………………………………Pain Relieve/fever reducer
Chlorpheniramine maleate 2mg ……………………………………Antihistamine
Dextromethorphan hydrobromide 10mg……………………….Cough suppressant
Phenylephrine hydrochloride 5mg………………………………...Nasal decongestant

Purposes

Active Ingredients (in each tablet) Purposes
Acetaminophen 250 mg…………………………………………………Pain Relieve/fever reducer
Chlorpheniramine maleate 2mg ……………………………………Antihistamine
Dextromethorphan hydrobromide 10mg……………………….Cough suppressant
Phenylephrine hydrochloride 5mg………………………………...Nasal decongestant

Uses: Temporarily relieves these symptoms due to a cold or flu:

• Minor aches and pains
• Headache
• Cough
• Sore throat
• Runny nose
• Nasal and sinus congestion
• Temporarily reduces fever

Warnings:

Liver Warning: This product contains acetaminophen. Severe liver damage may occur if you take:

• More than 8 tablets in 24 hours, which is the maximum daily amount for this product
• With other dugs containing acetaminophen
• 3 or more alcoholic drinks while using this product

Sore Throat Warning: If sore throat is severe, persists for more than 2 days, is accompanied by fever, headache, rash, nausea, or vomiting, consult a doctor promptly. Do not use to sedate children.

Do not use:

• With any other drug containing acetaminophen (prescription or nonprescription). If you are not sure whether a drug contains acetaminophen, ask a doctor or pharmacist.
• If you are now taking a prescription monoamine oxidase inhibitor (MAOI) (certain drugs for depression, psychiatric, or emotional conditions), or for 2 weeks after stopping the MAOI drug. If you do not know if your prescription drug contains an MAOI, ask a doctor or pharmacist before taking this product.
• If you have ever had an allergic reaction to this product or any of its ingredients
• In children under 12 years of age

Ask a doctor before use if you have:

• Liver disease
• Heart disease
• High blood pressure
• Thyroid disease
• Diabetes
• Glaucoma
• Cough with excessive phlegm (mucus)
• A breathing problem such as emphysema or chronic bronchitis
• Difficulty in urination due to enlargement of the prostate gland
• Persistent or chronic cough such as occurs with smoking, asthma, or emphysema
• A sodium restricted diet

Ask a doctor or pharmacist before use if you are:

• Taking the blood thinning medicine warfarin
• Taking sedatives or tranquilizers

When using this product:

• Do not exceed the recommended dosage
• May cause marked drowsiness
• Avoid alcoholic drinks
• Alcohol, sedatives, and tranquilizers may increase drowsiness
• Be careful when driving a motor vehicle or operating machinery
• Excitability may occur, especially in children

Stop use and ask a doctor if:

• Pain, cough, or nasal congestion gets worse or lasts more than 7 days
• Fever gets worse or lasts more than 3 days
• Redness or swelling is present
• New symptoms occur
• Cough comes back or occurs with rash or headache that lasts. These could be signs of a serious condition.
• Nervousness, dizziness, or sleeplessness occurs

If pregnant or breast-feeding, ask a health professional before use.

• Keep out of reach of children. In case of overdose, get medical help or contact a Poison Control Center right away. Quick medical attention is critical for adults as well as for children even if you do not notice any signs or symptoms.

Directions:

• Do not take more than the recommended dose
• Adults and children 12 years and over: take 2 tablets fully dissolved in 4oz. of water every four hours. Do not exceed 8 tablets in 24 hours or as directed by a doctor
• Children under 12 years: do not use

Other Information:

• Store at room temperature. Avoid excessive heat
Total Sodium: 406.73mg/tablet
Total Potassium: 3mg/tablet

Inactive Ingredients

Acesulfame potassium, sucralose, citric acid anhydrous, polysorbate 80, mannitol, orange flavor, PVP K-30, simethicone, sodium benzoate, sodium bicarbonate, color FD&C red #40